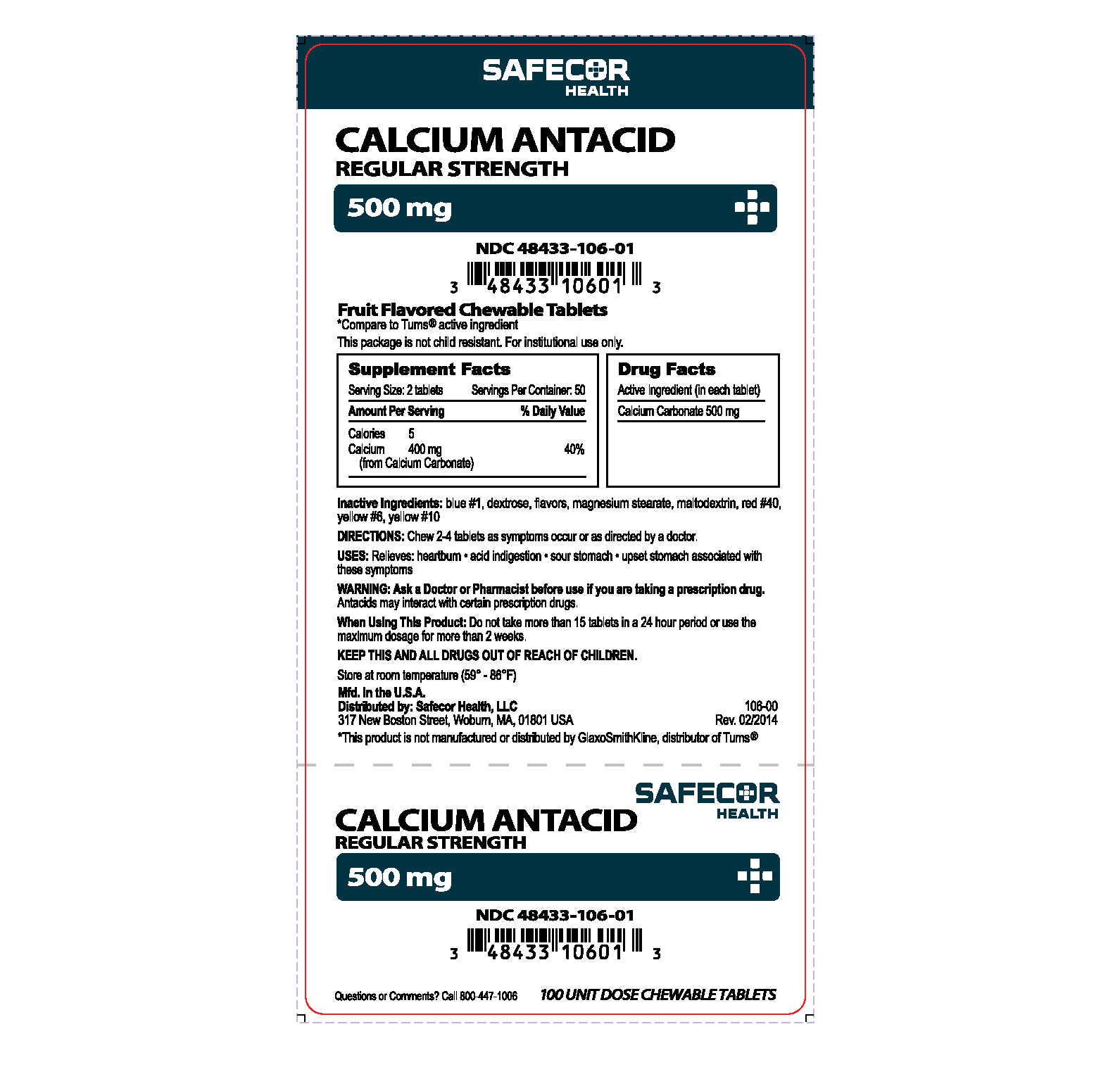 DRUG LABEL: Calcium Antacid
NDC: 48433-106 | Form: TABLET, CHEWABLE
Manufacturer: Safecor Health, LLC
Category: otc | Type: HUMAN OTC DRUG LABEL
Date: 20250108

ACTIVE INGREDIENTS: CALCIUM CARBONATE 500 mg/1 1
INACTIVE INGREDIENTS: FD&C BLUE NO. 1; DEXTROSE; MAGNESIUM STEARATE; MALTODEXTRIN; FD&C RED NO. 40; FD&C YELLOW NO. 6; D&C YELLOW NO. 10

Drug Facts

Active ingredient

Calcium Carbonate 500 mg

Purpose

Acid Indigestion, Heartburn, Sour & Upset Stomach

Uses

relieves

- heartburn
- acid indigestion
- sour stomach
- upset stomach associated with these symptoms

Ask a doctor or pharmacist before use if you are taking a prescription drug. Antacids may interact with certain prescription drugs.

When Using

do not take more than 15 tablets in a 24 hour period or use the maximum dosage of this product for more than two weeks.

Directions

- chew 2-4 tablets as symptoms occur, repeat hourly if needed

Other Information

- store at 59°-86°F
- do not use if imprinted safety seal under cap is broken or missing
- Calcium content per tablet: 200mg

Supplement Facts

- Serving size 2 tablets
- Servings per Container: 50
- Amount Per Serving
  Calories: 5
  Calcium: 400mg(40%DV)

Inactive Ingredients

Blue #1, dextrose, flavors, magnesium stearate, maltodextrin, red #40, yellow #6, yellow #10

Packaged and Distributed by:

Safecor Health, LLC
317 New Boston Street, Suite 100

Woburn, MA 01801

Package/Label Principal Display Panel

SAFECOR HEALTH

CALCIUM ANTACID

Regular Strength

500 mg

NDC 48433-106-01

Fruit Flavored Chewable Tablets

Compare to Tums ® Active Ingredient *

This package is not child resistant. For institutional use only.

This product is not manufactured or distributed by GlaxoSmithKline, distributor of Tums®

Questions or comments? Call 1-800-447-1006

100 Unit Dose Chewable Tablets